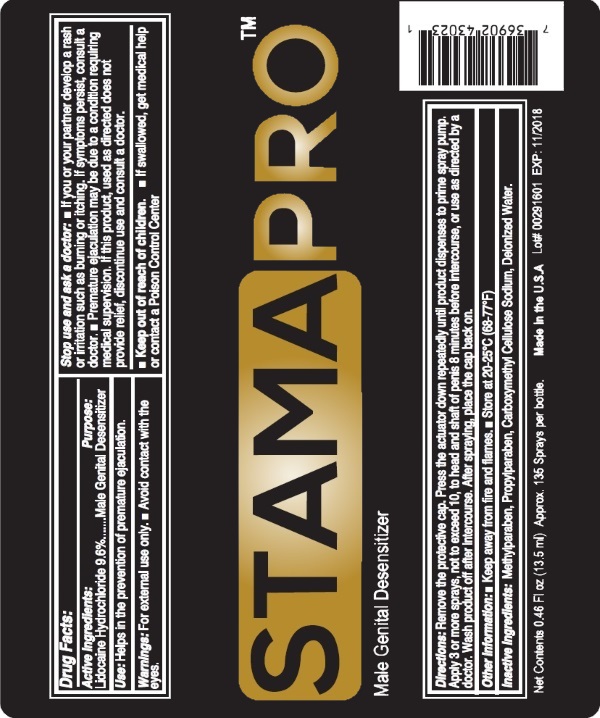 DRUG LABEL: STAMA PRO
NDC: 70107-302 | Form: SPRAY
Manufacturer: Cerno Pharmaceuticals
Category: otc | Type: HUMAN OTC DRUG LABEL
Date: 20170111

ACTIVE INGREDIENTS: LIDOCAINE 96 mg/1 mL
INACTIVE INGREDIENTS: METHYLPARABEN; PROPYLPARABEN; CARBOXYMETHYLCELLULOSE; WATER

ACTIVE INGREDIENT

Each milliliter contains
Active Ingredient | Purpose
Lidocaine Hydrochloride 9.6% | Male Genital Desensitizer

INACTIVE INGREDIENT

Methylparaben, Propylparaben, Carboxymethyl Cellulose Sodium, Deionized Water.

KEEP OUT OF REACH OF CHILDREN

If swallowed, get medical help or contact a Poison Control Center.

INDICATIONS & USAGE

Helps in the prevention of premature ejaculation.

WARNINGS

For external use only. ■ Avoid contact with the eyes.

Stop use and ask a doctor:

■ If you or your partner develop a rash or irritation such as burning or itching. If symptoms persist, consult a doctor.

■ Premature ejaculation may be due to a condition requiring medical supervision. If this product, used as directed does not provide relief, discontinue use and consult a doctor.

DOSAGE & ADMINISTRATION

Remove the protective cap. Press the actuator down repeatedly until product dispenses to prime spray pump.
Apply 3 or more sprays, not to exceed 10, to head and shaft of penis 8 minutes before intercourse, or use as directed by a
doctor. Wash product off after intercourse. After spraying, place the cap back on.

PURPOSE

Male Genital Desensitizer

Other Information

■ Keep away from fire and flames. ■ Store at 20-25°C (68-77°F)

Made in the U.S.A.